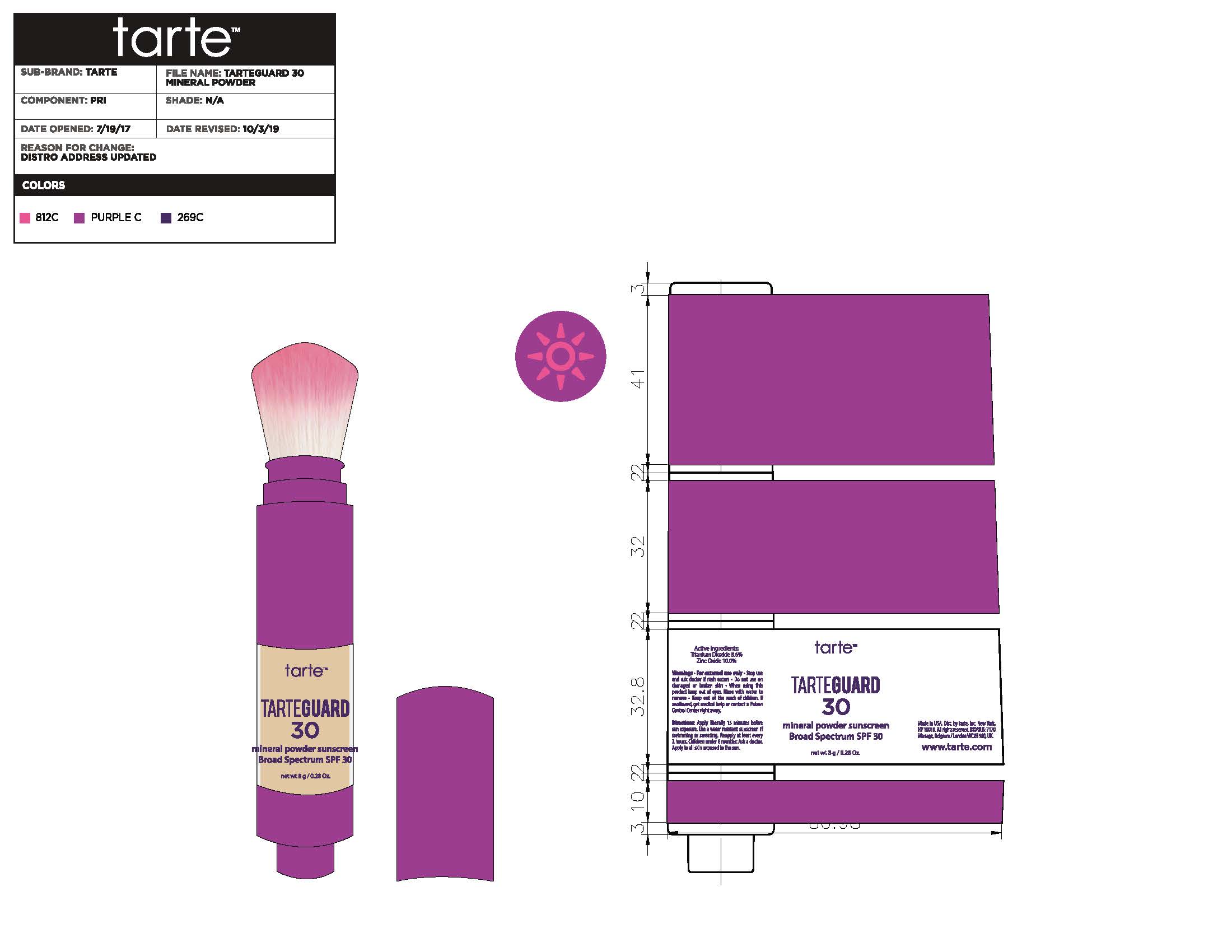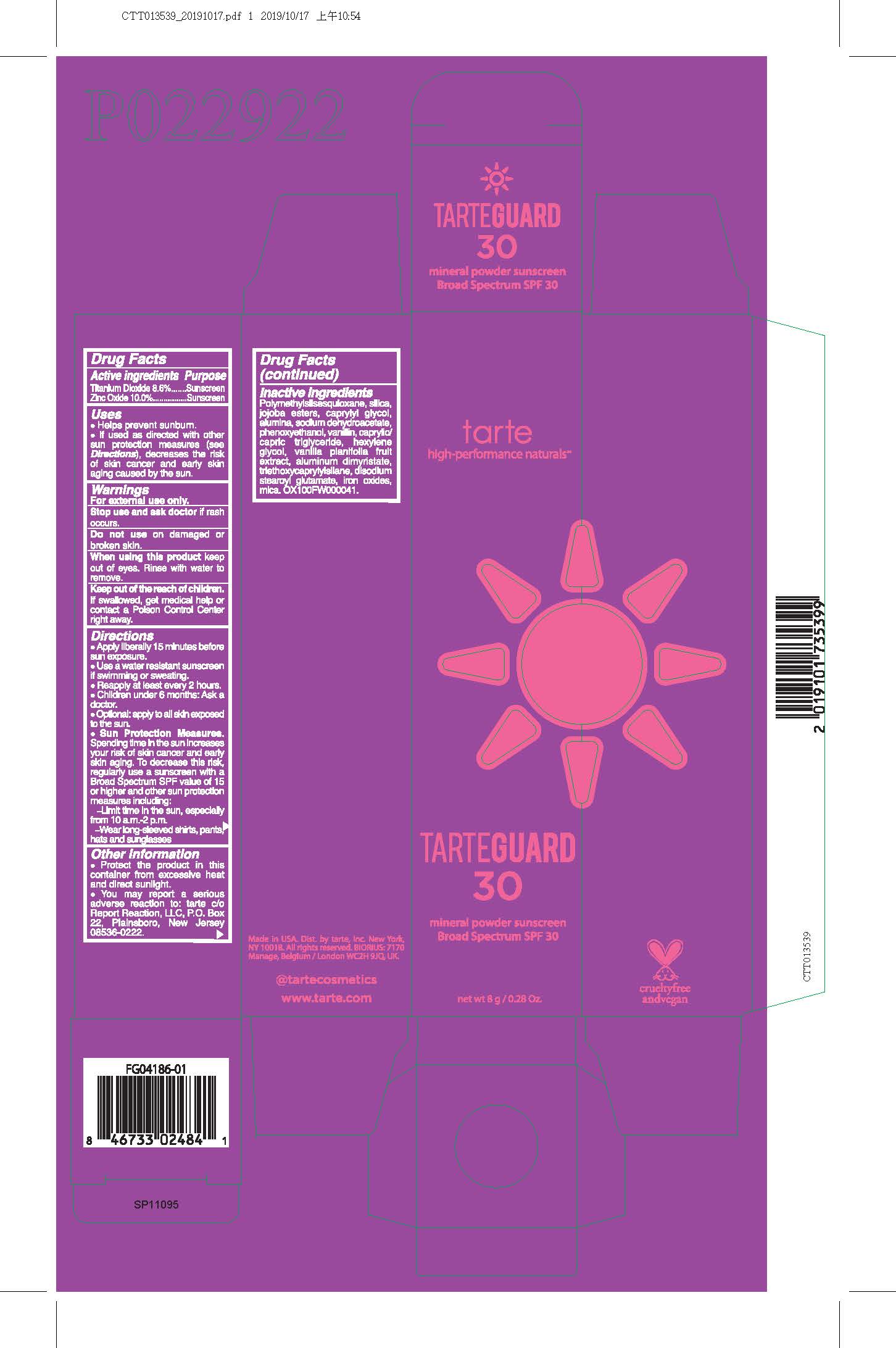 DRUG LABEL: Powder
NDC: 61354-043 | Form: POWDER
Manufacturer: Oxygen Development LLC
Category: otc | Type: HUMAN OTC DRUG LABEL
Date: 20220111

ACTIVE INGREDIENTS: ZINC OXIDE 10 g/100 g; TITANIUM DIOXIDE 8.6 g/100 g
INACTIVE INGREDIENTS: POLYMETHYLSILSESQUIOXANE (4.5 MICRONS) 73 g/100 g; SILICON DIOXIDE 5.35 g/100 g; POTASSIUM HYDROLYZED JOJOBA ESTERS 0.55 g/100 g

Active ingredients

Titanium Dioxide 8.6%

Zinc Oxide 10.0%

Purpose

Sunscreen

Uses

Helps prevent sunburn.

If used as directed with other sun protection measures (see Directions), decreases the risk of skin cancer and early skin aging caused by the sun.

Warnings

For external use only

Stop use

Stop use and ask doctor if rash occurs

When using

When using this product keep out of eyes. Rinse with water to remove.

Keep out of reach of children

Keep out of the reach of children. If swallowed, get medical help or contact a Poison Control Center right away.

Directions

Apply liberally 15 minutes before sun exposure.

Use a water resistant sunscreen if swimming or sweating.

Reapply at least every 2 hours.

Children unther 6 months: Ask a doctor.

Optional: apply to all skin exposed to the sun.

Sun Protection Measures. Spending time in the sun increases your risk of skin cancer early skin aging. To decrease this risk, regularly use a sunscreen with a Broad Spectrum SPF value of 15 or higher and other sun protection measures including:

Limit time in the sun, especially from 10 a.m - 2p.m.

Wear long - sleeved shirts, pants, hats and sunglasses.

Other information

Protect the prodcut in this container from excessive heat and direct sunlight.

You may report a serious adverse reaction to: tarte c/o Report Reaction, LLC, PO. Box 22, Plainsboro, New Jersey 08536-0222